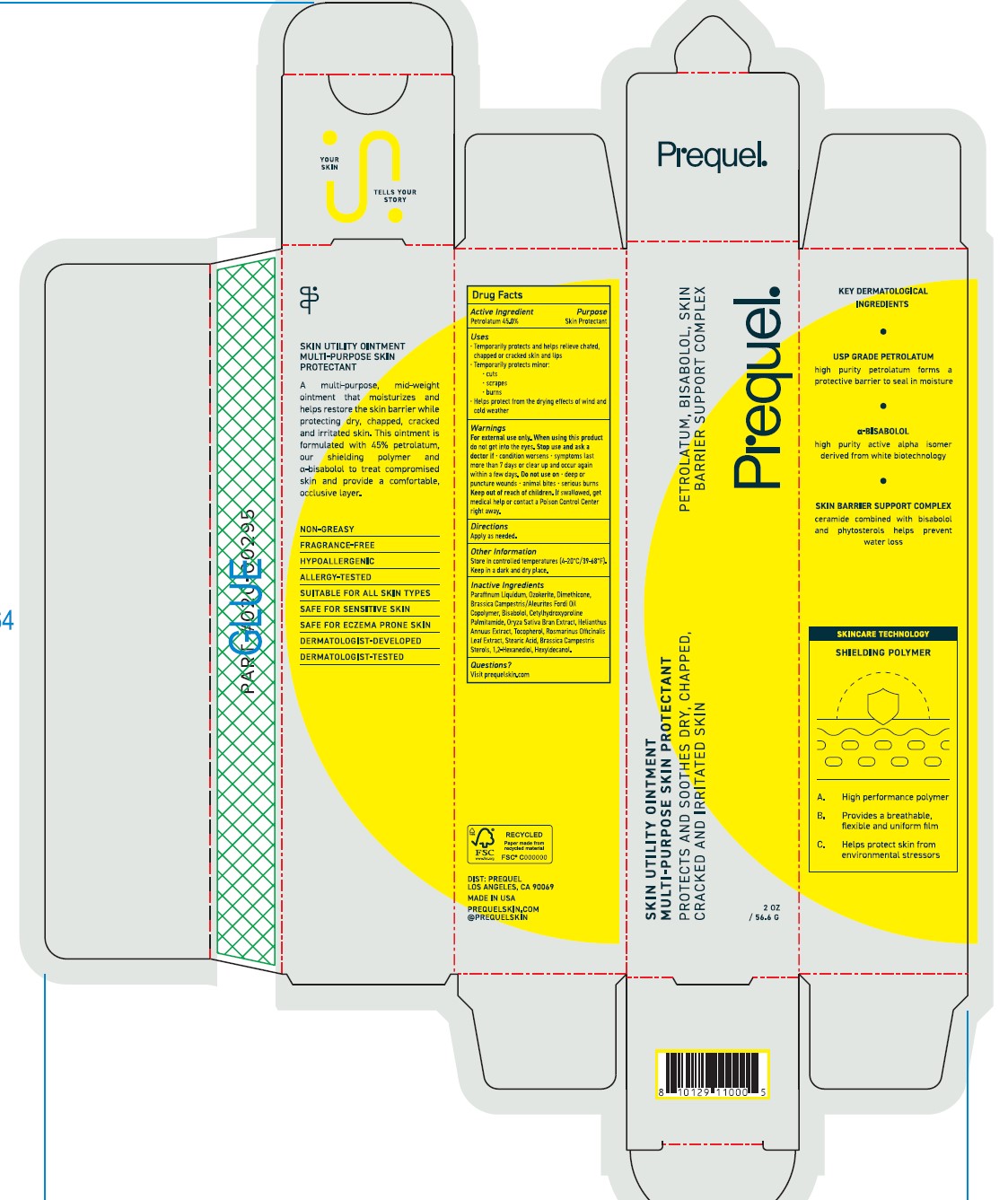 DRUG LABEL: Prequel Skin Utility Oint
NDC: 82800-018 | Form: OINTMENT
Manufacturer: The Center Brands, LLC
Category: otc | Type: HUMAN OTC DRUG LABEL
Date: 20251204

ACTIVE INGREDIENTS: PETROLATUM 45 g/100 g
INACTIVE INGREDIENTS: MINERAL OIL; DIMETHICONE; HEXYLDECANOL; CERESIN; RAPESEED STEROL; ROSEMARY; STEARIC ACID; SUNFLOWER SEED; TOCOPHEROL; 1,2-HEXANEDIOL; BRASSICA RAPA SUBSP. OLEIFERA OIL; LEVOMENOL; CETYLHYDROXYPROLINE PALMITAMIDE; RICE BRAN

DRUG FACTS

Purpose

Skin Protectant

Active Ingredients

Petrolatum 45.00%

Uses

•Temporarily protects and helps releive chafed, chapped or craked skin and lips

•Temporarily protects minor:

•cuts

•scrapes

•burns

•Helps protect form the drying effects of wind and cold weather

Warnings

Fox external use only.

When using this product do not get into eyes

Stop use and ask a doctor if

- condition worsens
- symptoms last more than 7 days or clear up and occur again within a few days. Do not use on • deep or puncture woulds • animal bites • serious burns.

Keep out of reach of children. If swalled, get medical help or contact a Poison Control Center right away.

Directions

Apply as needed.

Inactive Ingredients

Parrafinum Liquidum, Ozokerite, Dimethicone, Brassica Campestric/Aleuites Fordi Oil Copolymer, Bisabolol, Cetylhydroxyproline Palmitamide, Oryza Sativa Bran Extract, Helianthus Annuus Extract, Tocopherol, Rosmarinus Officinalis Leaf Extract, Stearic Acid, Brassica Campestris Sterols, 1,2-Hexanediol, Hexyldecanol

Other Information

Visit prequelskin.com